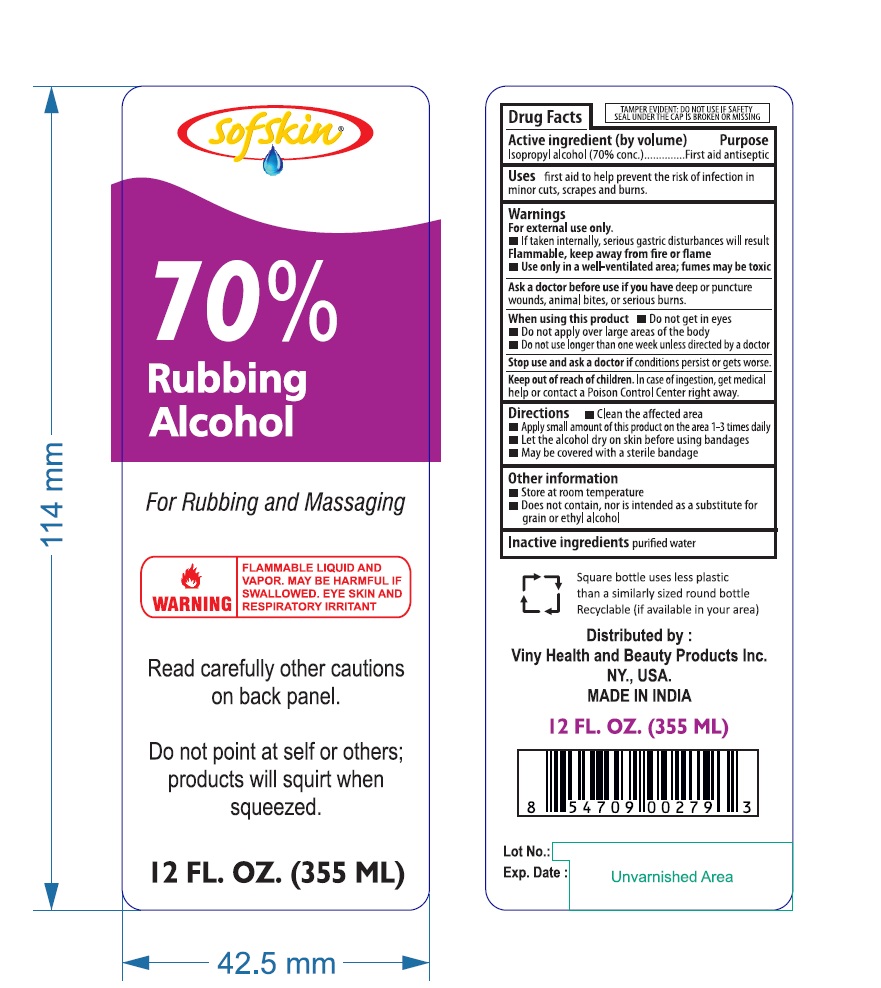 DRUG LABEL: RUBBING ALCOHOL 70 PERCENT
NDC: 76436-323 | Form: SOLUTION
Manufacturer: Viny Health and Beauty Products Inc
Category: otc | Type: HUMAN OTC DRUG LABEL
Date: 20250701

ACTIVE INGREDIENTS: ISOPROPYL ALCOHOL 70 mL/100 mL
INACTIVE INGREDIENTS: WATER

VHB (as PLD) - RUBBING ALCOHOL 70 PERCENT (76436-320)

Active ingredient

ISOPROPYL ALCOHOL 70%

Purpose

FIRST AID ANTISEPTIC

Uses

FIRST AID TO HELP PREVENT THE RISK IN:

- MINOR CUTS
- SCRAPES BURNS

Keep Out of Reach of Children

IF SWALLOWED, GET MEDICAL HELP OR CONTACT A POISON CONTROL CENTER RIGHT AWAY.

FOR RUBBING AND MASSAGING: CAUTION - DO NOT APPLY TO IRRITATED SKIN OR IF EXCESSIVE IRRITATION DEVELOPS. AVOID GETTING INTO THE EYES OR ON MUCOUS MEMBRANES.

WARNINGS

For external use only.

- FLAMMABLE, KEEP AWAY FROM FIRE OR FLAME, HEAT, SPARK, ELECTRICAL.

ASK A DOCTOR BEFORE USE IF YOU HAVE

- DEEP PUNCTURE WOUNDS SERIOUS BURNS

WHEN USING THIS PRODUCT

- DO NOT GET INTO EYES
- DO NOT APPLY OVER LARGE AREAS OF THE BODY.
- DO NOT USE LONGER THAN 1 WEEK UNLESS DIRECTED BY A DOCTOR.

STOP USE AND ASK A DOCTOR IF

- CONDITION PERSISTS OR GET WORSE.

Directions

- CLEAN THE AFFECTED AREA.
- APPLY A SMALL AMOUNT OF THIS PRODUCT ON THE AREA 1 TO 3 TIMES DAILY
- MAY BE COVERED WITH A STERILE BANDAGE
- IF BANDAGED, LET DRY FIRST.

OTHER INFORMATION

- DOES NOT CONTAIN, NOR IS INTENDED AS A SUBSTITUTE FOR GRAIN OR ETHYL ALCOHOL

- WILL PRODUCE SERIOUS GASTRIC DISTURBANCES IF TAKEN INTERNALLY.

Inactive Ingredient

WATER